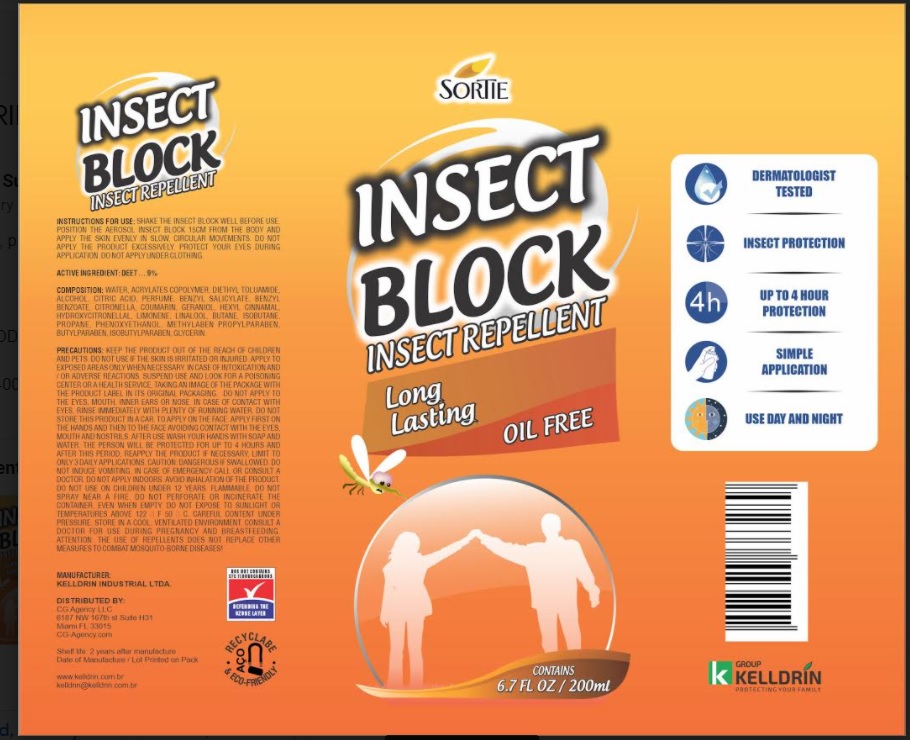 DRUG LABEL: INSECT REPELLENT INSECT BLOCK
NDC: 80214-005 | Form: AEROSOL
Manufacturer: MOD DESIGN BUILD
Category: otc | Type: HUMAN OTC DRUG LABEL
Date: 20210326

ACTIVE INGREDIENTS: DIETHYLTOLUAMIDE 9 g/100 mL
INACTIVE INGREDIENTS: ALCOHOL; WATER; BIS-DIGLYCERYL POLYACYLADIPATE-2; ANHYDROUS CITRIC ACID; GLYCERIN; BUTANE; ISOBUTANE; PROPANE

Active Ingredient

DEET - 9%

Purpose

Insect repellent

Use

-Shake the Insect Block Aerosol well before use.
- Position the aerosol Insect Block at a distance of 15 cm from the body and the skin
evenly in slow and circular movements.
- Do not apply the product excessively.
- Protect your eyes during application.
- Do not apply under clothing.

Warnings

- Keep the product out of the reach of children and pets.
-Do not use if the skin is irritated or injured.
-Apply to exposed areas only when necessary.
- In case of intoxication and/or adverse reactions, suspend use and look for a poisoning center or
health service, taking an image of the package with the product label in its original packaging.
- Do not apply to the eyes, mouth, inner ears or nose.
-Watch your eyes, in case of contact with eyes, rinse immediately with plenty of running water.
-Do not store this product in a car.
-To apply on the face: apply first the product on the hands and then to the face, avoiding contact
with the eyes, mouth and nostrils.
- After use wash your hands with soap and water.
- The person will be protected for up to 4 hours and after this period.
Reapply the product if necessary.
Limit to only 3 daily applications.
Caution: dangerous if swallowed do not induce vomiting.
In case of emergency call or consult a doctor.
Do not apply indoors.
Avoid inhalation of the product.
Do not use on children under 12 years.
Flammable, do not spray near fire.
Do not spray near a fire.
Do not perforate or incinerate the container.
Even when empty, do not expose to the sunlight or the temperature above 122°F and 5o°c.
Careful content under pressure store in a cool ventilated environment.
Consult a doctor for use during pregnancy and breastfeeding.
Attention the use of repellents does not replace other measures to combat mosquito-borne diseases.

Inactive ingredients

WATER, ACRYLATE$ COPOLYMER, DIETHYL TOLUAMIDE, ALCOHOL, CITRIC ACID, PERFUME, BENZYL
SALICYLATE, BENZYL BENZOATE, CITRONELLA, COUMARIN, GERANIOL, HEXYL CINNAMAL,
HYDROXYCITRONELLAL, LIMONENE, LINALOOL, BUTANE, ISOBUTANE, PROPANE, PHENOXYETHANOL,
METHYLPARABEN, PROPYLBARABEN, BUTYLPARABEN, ISOBUTYLPARABEN, GLYCERIN.